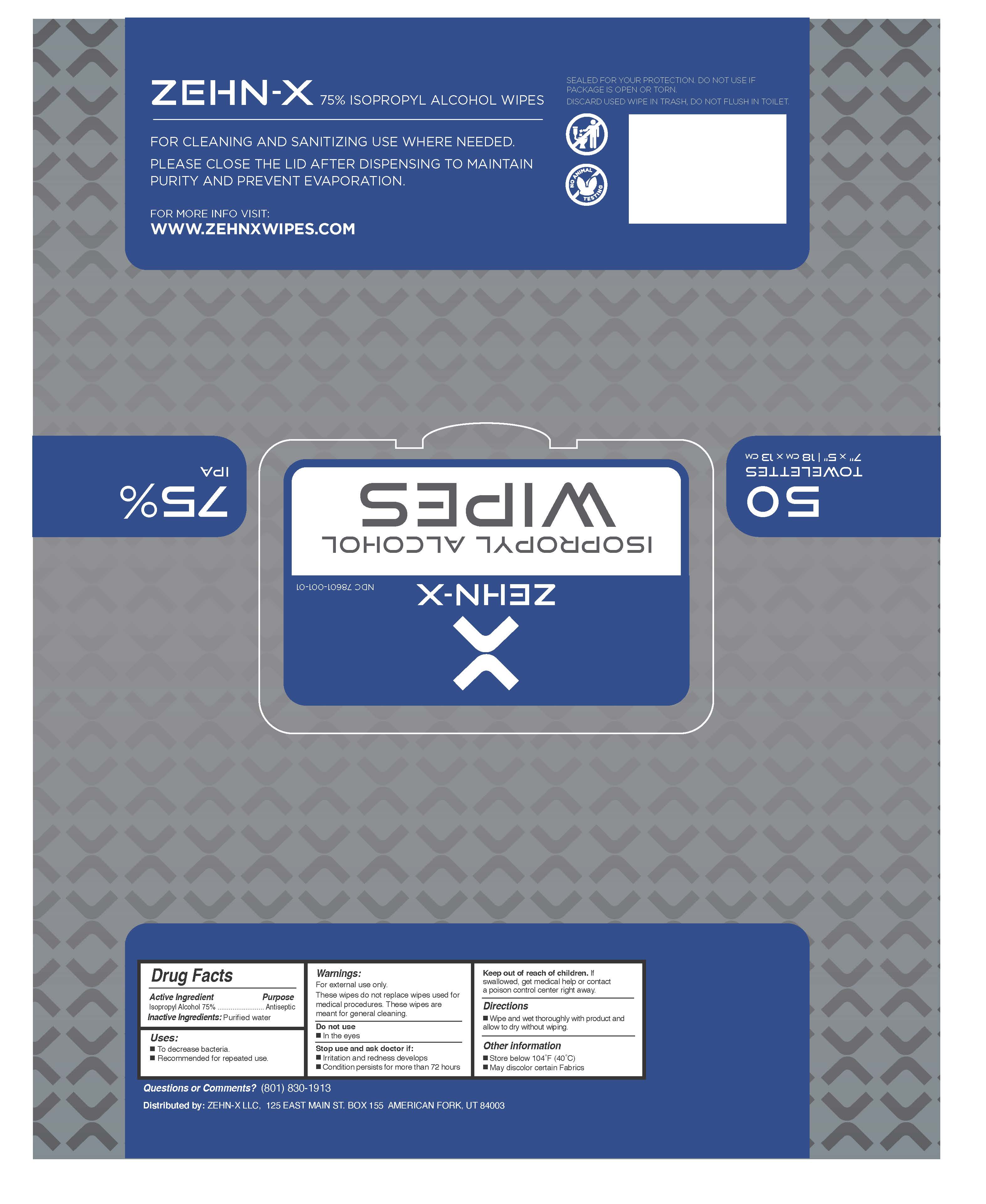 DRUG LABEL: ANTISEPTIC SANITIZING WIPES
NDC: 75714-003 | Form: CLOTH
Manufacturer: HANGZHOU CLEAN NONWOVEN CO.,LTD
Category: otc | Type: HUMAN OTC DRUG LABEL
Date: 20210708

ACTIVE INGREDIENTS: ISOPROPYL ALCOHOL 75 g/100 g
INACTIVE INGREDIENTS: WATER

75714-003 ANTISEPTIC SANITIZING WIPES 75% Isopropyl Alcohol

Active Ingredient

lsopropyl Alcohol75%.

Purpose

Antiseptic

USE

To decrease bacteria.
Recommended for repeated use.

Warning

Do not use
ln the eyes
For external use only.
These wipes do not replace wipes used for
medical procedures.These wipes are
meant for general cleaning.
Stop use and ask doctor if:
lrritation and redness develops
Condition persists for more than 72 hours

Keep out of reach of children. If
swallowed, get medical help or contact
a poison control center right away.

Directions

■Wet hands thoroughly with product and
allow to dry without wiping.

Inactive ingredients

Purified water